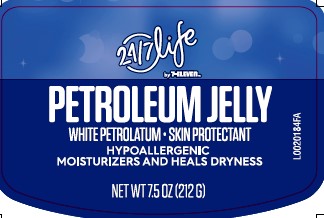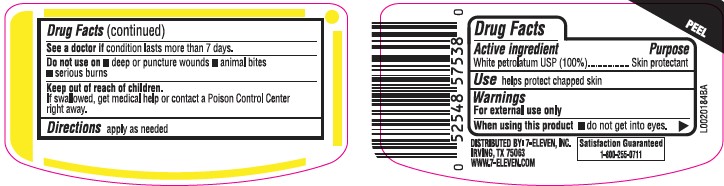 DRUG LABEL: Petroleum
NDC: 10202-069 | Form: JELLY
Manufacturer: 7-Select
Category: otc | Type: HUMAN OTC DRUG LABEL
Date: 20260129

ACTIVE INGREDIENTS: PETROLATUM 1 g/1 g

24/7 Life 069.001/069AA
Petroleum Jelly

Active ingredient

White petrolatum USP (100%)

Purpose

Skin protectant

Use

help protect chapped skin

Warnings

For external use only

When using this product

- do not get into eyes

See a doctor if

condition lasts more than 7 days

Do not use on

- deep or puncture wounds
- animal bites
- serious burns

Keep out of reach of children.

If swallowed, get medical help or contact a Poison Control Center right away.

Directions

apply as needed

inactive ingredients

None

Adverse Reactions

DISTRIBUTED BY: 7-ELEVEN, INC.

IRVING, TX 75063

WWW.7-ELEVEN.COM

SATISFACTION GUARANTEED

1-800-255-0711

Principal Panel Display

24/7 LIFE

by 7-ELEVEN™

PETROLEUM JELLY

WHITE PETROLATUM - SKIN PROTECTANT

HYPOALLERGENIC

MOISTURIZERS AND HEALS DRYNESS

NET WT 7.5 OZ (212 G)